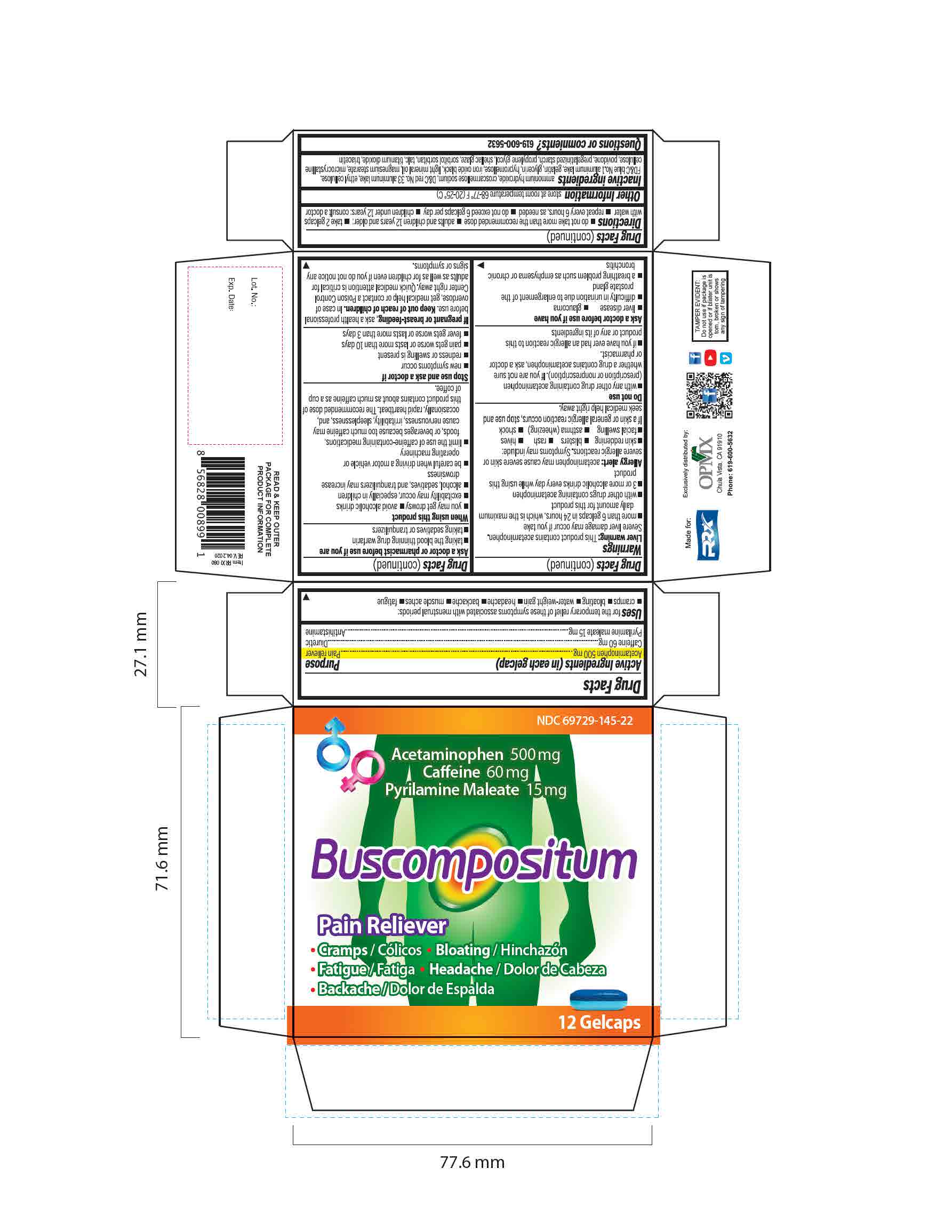 DRUG LABEL: Acetaminophen 500mg Caffeine 60mg Pyrilamine maleate 15mg
NDC: 69729-145 | Form: TABLET
Manufacturer: OPMX LLC
Category: otc | Type: HUMAN OTC DRUG LABEL
Date: 20201116

ACTIVE INGREDIENTS: CAFFEINE 60 mg/1 1; PYRILAMINE MALEATE 15 mg/1 1; ACETAMINOPHEN 500 mg/1 1
INACTIVE INGREDIENTS: MAGNESIUM STEARATE; HYPROMELLOSES; D&C RED NO. 33; GLYCERIN; FERROSOFERRIC OXIDE; LIGHT MINERAL OIL; POVIDONE; HYDROXYETHYL CELLULOSE, UNSPECIFIED; FD&C BLUE NO. 1; GELATIN; STARCH, CORN; SHELLAC; SORBITOL; TALC; TRIACETIN; MICROCRYSTALLINE CELLULOSE; PROPYLENE GLYCOL; TITANIUM DIOXIDE; CROSCARMELLOSE SODIUM

Buscompositum
Acetaminophen 500mg, Caffeine 60mg, Pyrilamine Maleate 15mg

ACTIVE INGREDIENT

Acetaminophen 500mg

Caffeine 60mg

Pyrilamine maleate 15mg

INACTIVE INGREDIENT

ammonium hydroxide, croscarmellose sodium, D&C red No. 33 aluminum lake, ethyl cellulose, FD&C blue No. 1 aluminum lake, gelatin, glycerin, hypromellose, iron oxide black, light mineral oil, magnesium stearate, microcrystalline cellulose, povidone, pregelatinised starch, propylene glycol, shellac glaze, sorbitol sorbitan, talc, titanium dioxide, triacetin

DOSAGE AND ADMINISTRATION

- Do not take more than the recommended dose
- Adults and children 12 years and over: take 2 gelcaps with water, repeat every 6 hours, as needed; do not exceed 6 gelcaps per day
- Children under 12 years: consult a doctor

INDICATIONS AND USAGE

For the temporary relief of these symptoms associated with menstrual periods:

Cramps, bloating water-weight gain, headache, backache, muscle aches, fatigue.

WARNINGS

Liver warning: This product contains acetaminophen. Severe liver damage may occur if you take more than 6 gelcaps in 24 hours, which is the maximum daily amount for this product, with other drugs contains acetaminophen, 3 or more alcoholic drinks every day while using this product.

Allergy alert: Acetaminophen may cause severe skin reactions or severe allergic reactions. Symptoms may include: skin reddening, blisters, rash, hives, facial swelling, asthma (wheezing), shock. If a skin or general allergic reaction occurs, stop use and seek medical help right away.

Do not use with any other drug containing acetaminophen (prescription or nonprescription). If you are not sure whether a drug contains acetaminophen, ask a doctor or pharmacist, if you have ever had an allergic reaction to this product or any of its ingredients.

Ask a doctor before use if you have liver disease, glaucoma, difficulty in urination due to enlargement of the prostate gland, a breathing problem such as emphysema or chronic bronchitis.

Ask a doctor or pharmacist before use if you are taking the blood thinning drug warfarin, taking sedatives or tranquilizers.

When using this product, you may get drowsy, avoid alcoholic drinks, excitability may occur, especially in children, alcohol, sedatives, and tranquilizers may increase drowsiness, be careful when driving a motor vehicle or operating machinery, limit the use of caffeine-containing medications, foods, or beverages because too much caffeine may cause nervousness, irritability, sleeplessness, and, occasionally, rapid heartbeat. The recommended dose of this product contains about as much caffeine as a cup of coffee.

Stop use and ask a doctor if new symptoms occur, redness or swelling is present, pain gets worse or lasts for more than 10 days, fever gets worse or lasts for more than 3 days.

If pregnant or breast-feeding, ask a health professional before use.

Keep out of reach of children

Overdose Warning: In case of overdose, get medical help or contact a Poison Control Center right away. Quick medical attention is critical for adults as well as for children even if you do not notice any signs or symptoms.

PURPOSE

Pain reliever

Nighttime sleep-aid

OTHER SAFETY INFORMATION

Store at room temperature between 20-25 ºC (68-77 ºF)